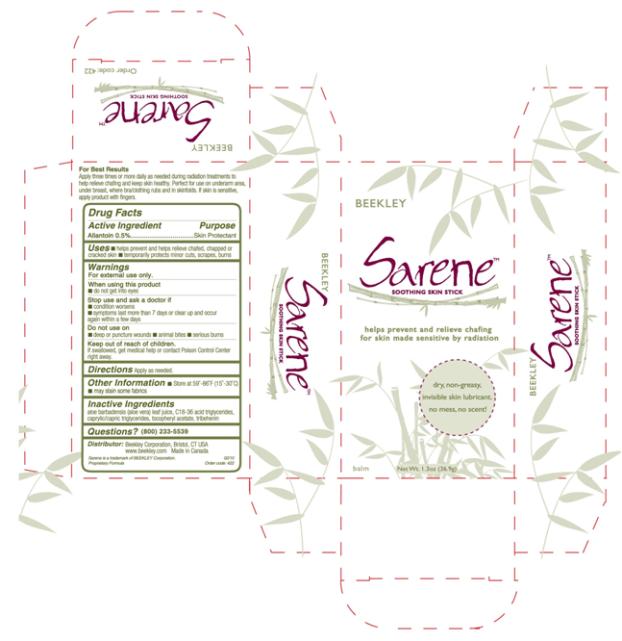 DRUG LABEL: Sarene Soothing Skin
NDC: 52319-001 | Form: STICK
Manufacturer: Beekley Corporation
Category: otc | Type: HUMAN OTC DRUG LABEL
Date: 20100410

ACTIVE INGREDIENTS: ALLANTOIN 5 mg/1 g
INACTIVE INGREDIENTS: ALOE VERA LEAF; MEDIUM-CHAIN TRIGLYCERIDES; .ALPHA.-TOCOPHEROL ACETATE, D-; TRIBEHENIN

Sarene Soothing Skin Stick

Active Ingredient:

Allantoin 0.5%

Purpose:

Skin Protectant

Uses:

- helps prevent and helps relieve chafed, chapped or cracked skin
- temporarily protects minor cuts, scrapes, burns

Warnings

For external use only.

When using this product

- do not get into eyes

Stop use and ask a doctor if

- condition worsens
- symptoms last more than 7 days or clear up and occur again within a few days

Do not use on

- deep or puncture wounds
- animal bites
- serious burns

Keep out of reach of children.

If swallowed, get medical help or contact Poison Control Center right away.

Directions

Apply as needed.

Other Information

- Store at 59º – 86º F (15º - 30º C)
- may stain some fabrics

Inactive Ingredients

aloe barbadensis (aloe vera) leaf juice, C18-36 acid triglycerides, caprylic/capric triglycerides, tocopheryl acetate, tribehenin

Questions

+1 (800) 233-5539

Distributor:
Beekley Corporation, Bristol, CT
Made in Canada

PRINCIPAL DISPLAY PANEL

BEEKLEY
Sarene™
SOOTHING SKIN STICK
helps prevent and relieve chafing
for skin made sensitive by radiation
dry, non-greasy,
invisible skin lubricant.
no mess, no scent!
balm
NET WT. 1.3 oz (36.9 g)